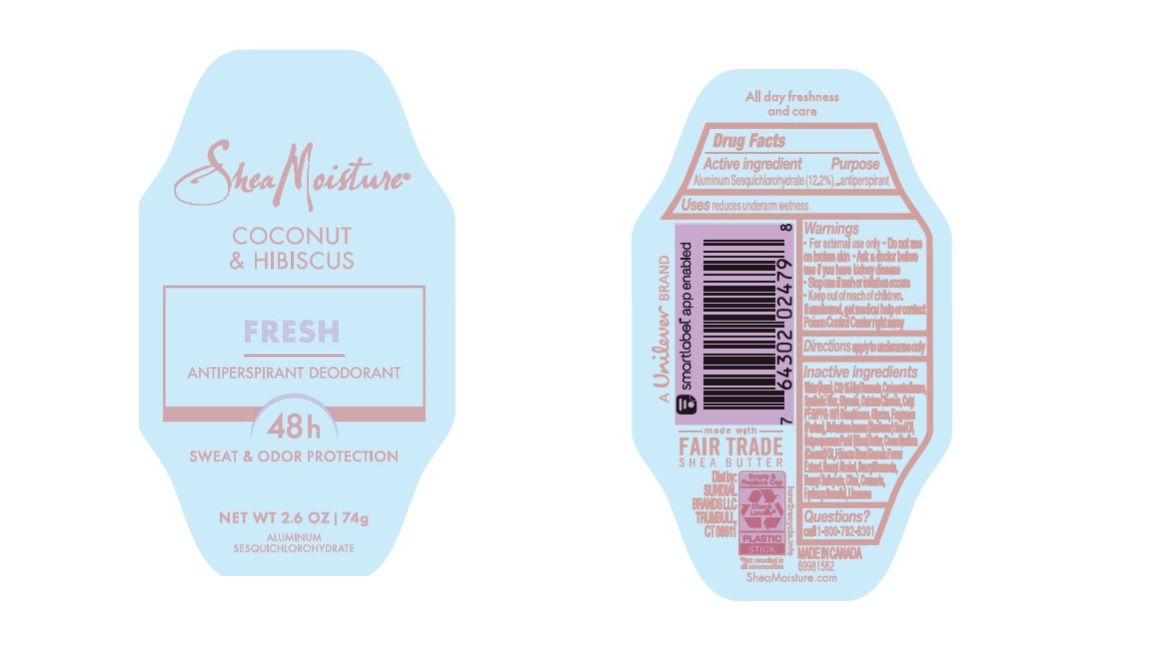 DRUG LABEL: Dove
NDC: 64942-2148 | Form: STICK
Manufacturer: Conopco Inc. d/b/a/ Unilever
Category: otc | Type: HUMAN OTC DRUG LABEL
Date: 20241024

ACTIVE INGREDIENTS: ALUMINUM SESQUICHLOROHYDRATE 12.2 g/100 g
INACTIVE INGREDIENTS: COCONUT OIL; BENZYL BENZOATE; HYDROXYCITRONELLAL; LIMONENE, (+)-; CYCLOMETHICONE 5; CITRAL; CALCIUM CHLORIDE; WATER; ALKYL (C12-15) BENZOATE; SYNTHETIC WAX (1200 MW); GLYCERIN; CETYL PEG/PPG-10/1 DIMETHICONE (HLB 4); GLYCINE; SUNFLOWER OIL; SHEA BUTTER; BENZYL ALCOHOL; HIBISCUS ROSA-SINENSIS FLOWER; COUMARIN; BENZYL SALICYLATE

Shea Moisture Coconut & Hibiscus Fresh 48h Antiperspirant Deodorant

Drug Facts

Active ingredient

Aluminum Sesquichlorohydrate (12.2)

Purpose

antiperspirant

Uses

reduces underarm wetness

Warnings

• For external use only.
• Do not use on broken skin .
• Ask a doctor before use if you have kidney disease.
• Stop use if rash or irritation occurs.

• Keep out of reach of children.

If swallowed, get medical help or contact a Poison Control Center right away.

Directions

apply to underarms only

Inactive ingredients

Water (Aqua), C12-15 Alkyl Benzoate, Cyclopentasiloxane, Synthetic Wax, Glycerin, Calcium Chloride, Cetyl PEG/PPG-10/1 Dimethicone, Glycine, Fragrance (Parfum), Helianthus Annuus (Sunflower) Seed Oil, Butyrospermum Parkii (Shea) Butter, Cocos Nucifera (Coconut) Oil, Hibiscus Rosa Sinensis Flower Extract, Benzyl Alcohol, Benzyl Benzoate, Benzyl Salicylate, Citral, Coumarin, Hydroxycitronellal, Limonene.

Questions?

Call 1-800-761-3683